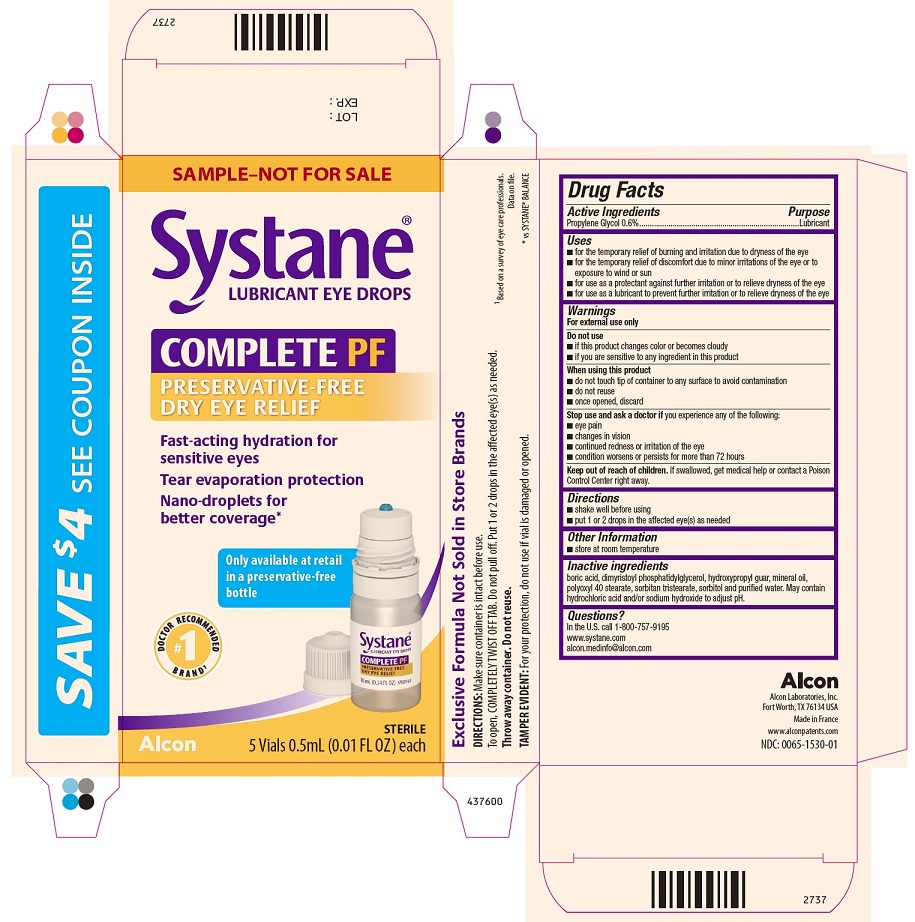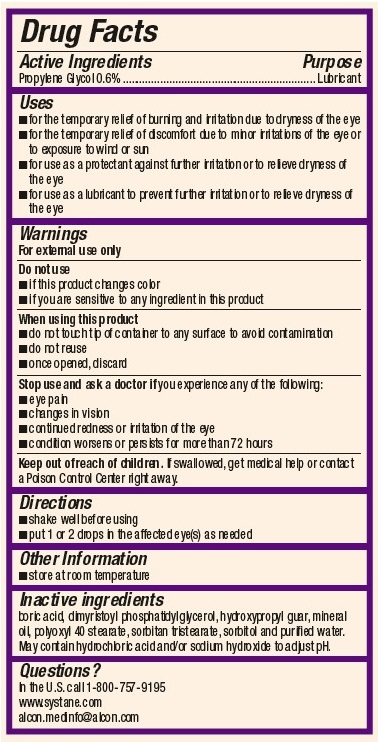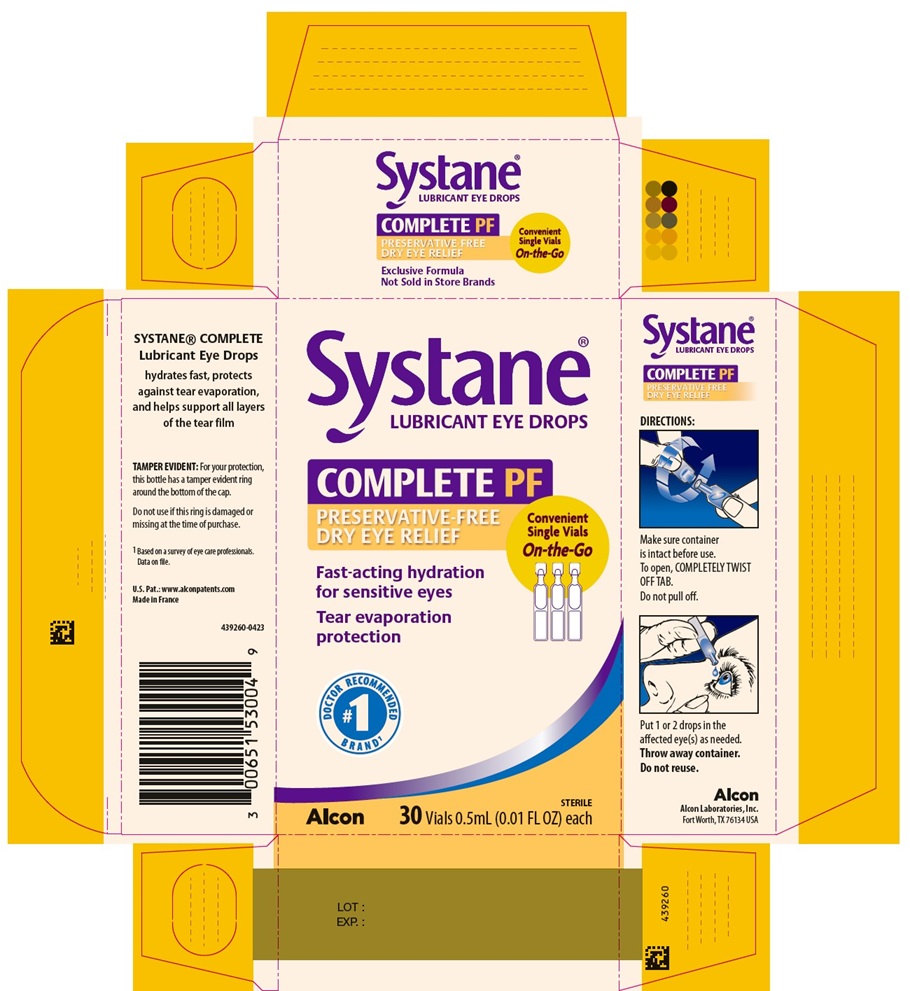 DRUG LABEL: Systane COMPLETE PF
NDC: 0065-1530 | Form: EMULSION
Manufacturer: Alcon Laboratories, Inc.
Category: otc | Type: HUMAN OTC DRUG LABEL
Date: 20231214

ACTIVE INGREDIENTS: Propylene Glycol .06 mg/1 mL
INACTIVE INGREDIENTS: Boric Acid; Dimyristoylphosphatidylglycerol, Dl-; Guaraprolose (3500 Mpa.S At 1%); Mineral Oil; Polyoxyl 40 Stearate; Sorbitan Tristearate; Sorbitol; Water; Hydrochloric Acid; Sodium Hydroxide

SYSTANE COMPLETE PF PRESERVATIVE FREE- Propylene Glycol Emulsion
Drug Facts

Active Ingredients | Purpose
Propylene Glycol 0.6% | Lubricant

Uses

- for the temporary relief of burning and irritation due to dryness of the eye
- for the temporary relief of discomfort due to minor irritations of the eye or to exposure to wind or sun
- for use as a protectant against further irritation or to relieve dryness of the eye
- for use as a lubricant to prevent further irritation or to relieve dryness of the eye

Warnings

For external use only

Do not use

- if this product changes color or becomes cloudy
- if you are sensitive to any ingredient in this product

When using this product

- do not touch tip of container to any surface to avoid contamination
- do not reuse
- once opened, discard

Stop use and ask a doctor if you experience any of the following:

- eye pain
- changes in vision
- continued redness or irritation of the eye
- condition worsens or persists for more than 72 hours

Keep out of reach of children.
If swallowed, get medical help or contact a Poison Control Center right away.

Directions

- shake well before using
- put 1 or 2 drops in the affected eye(s) as needed

Other Information

- store at room temperature

Inactive Ingredients

boric acid, dimyristoyl phosphatidylglycerol, hydroxypropyl guar, mineral oil, polyoxyl 40 stearate, sorbitan tristearate, sorbitol and purified water. May contain hydrochloric acid and/or sodium hydroxide to adjust pH.

Questions?

In the U.S. call 1-800-757-9195
www.systane.com
alcon.medinfo@alcon.com

437600

PRINCIPAL DISPLAY PANEL

Alcon Laboratories, Inc.
Fort Worth, TX 76134 USA
Made in France
www.alconpatents.com

NDC: 0065-1530-01
437600

SAMPLE-NOT FOR SALE
Systane®
LUBRICANT EYE DROP
COMPLETE PF
PRESERVATIVE-FREE
DRY EYE RELIEF
Fast-acting hydration for sensitive eyes
Tear evaporation protection
Nano-droplets for better coverage*
Only available at retail in a preservative-free bottle
#1 DOCTOR RECOMMENDED BRAND^1
Alcon
STERILE
5 Vials 0.5 mL (0.01 FL OZ) each
Side Panel:
Exclusive Formula Not Sold in Store Brands
DIRECTIONS: Make sure container is intact before use.
To open, COMPLETELY TWIST OFF TAB. Do not pull off. Put 1 or 2 drops in the affected eye(s) as needed.
Throw away container. Do not reuse.
TAMPER EVIDENT: For your protection, do not use if vial is damaged or opened.
437600
^1Based on a survey of eye care professionals.
Data on file.
*vs SYSTANE® BALANCE
LOT :
EXP:
2737

NDC: 0065-1530-04
439260

Systane®
LUBRICANT EYE DROPS
COMPLETE PF
PRESERVATIVE-FREE
DRY EYE RELIEF
Convenient
Single Vial
On-the-Go
Fast-acting hydration for sensitive eyes
Tear evaporation protection
DOCTOR RECOMMENDED #1 BRAND^1
Alcon
Sterile
30 Vials 0.5mL (0.01 FL OZ) each
Side Panel:
DIRECTIONS:
Make sure container is intact before use.
To open, COMPLETELY TWIST OFF TAB.
Do not pull off.
Put 1 or 2 drops in the affected eye(s) as needed.
Throw away container. Do not reuse.
Alcon
Alcon Laboratories, Inc.
Fort Worth, TX 76134 USA
SYSTANE® COMPLETE
Lubricant Eye Drops
hydrates fast, protects against tear evaporation, and helps support all layers of the tear film
TAMPER EVIDENT: For your protection, this bottle has a tamper evident ring around the bottom of the cap.
Do not use if this ring is damaged or missing at the time of purchase.
^1Based on a survey of eye care professionals.
Data on file.
U.S. Pat.:www.alconpatents.com
Made in France
439260-0423
LOT :
EXP.:
439260